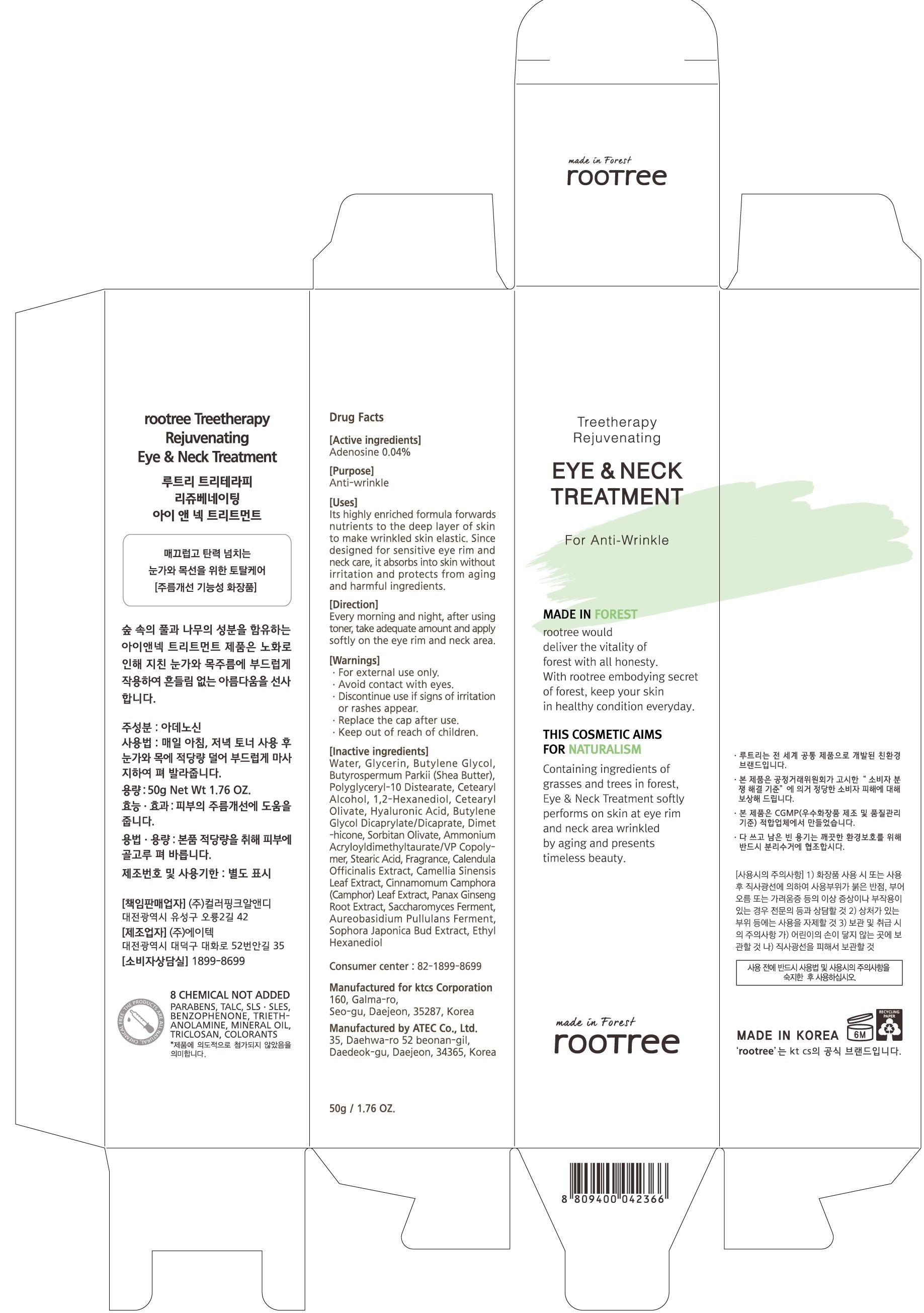 DRUG LABEL: rootree Treetherapy Rejuvenating Eye and Neck Treatment
NDC: 72441-110 | Form: LIQUID
Manufacturer: KTCS Corporation
Category: otc | Type: HUMAN OTC DRUG LABEL
Date: 20190624

ACTIVE INGREDIENTS: Adenosine 0.02 g/50 g
INACTIVE INGREDIENTS: Water; Glycerin

ACTIVE INGREDIENT

Active ingredients: Adenosine 0.04%

INACTIVE INGREDIENT

Inactive ingredients:

Water, Glycerin, Butylene Glycol, Butyrospermum Parkii (Shea Butter), Polyglyceryl-10 Distearate, Cetearyl Alcohol, 1,2-Hexanediol, Cetearyl Olivate, Hyaluronic Acid, Butylene Glycol Dicaprylate/Dicaprate, Dimethicone, Sorbitan Olivate, Ammonium Acryloyldimethyltaurate/VP Copolymer, Stearic Acid, Fragrance, Calendula Officinalis Extract, Camellia Sinensis Leaf Extract, Cinnamomum Camphora (Camphor) Leaf Extract, Panax Ginseng Root Extract, Saccharomyces Ferment, Aureobasidium Pullulans Ferment, Sophora Japonica Bud Extract, Ethyl Hexanediol

PURPOSE

Purpose: Anti-wrinkle

WARNINGS

For external use only.

Avoid contact with eyes.

Discontinue use if signs of irritation or rashes appear.

Replace the cap after use.

Keep out of reach of children

KEEP OUT OF REACH OF CHILDREN

Uses

Its highly enriched formula forwards nutrients to the deep layer of skin to make wrinkled skin elastic. Since designed for sensitive eye rim and neck care, it absorbs into skin without irritation and protects from aging and harmful ingredients.

Directions

Every morning and night, after using toner, take adequate amount and apply softly on the eye rim and neck area.